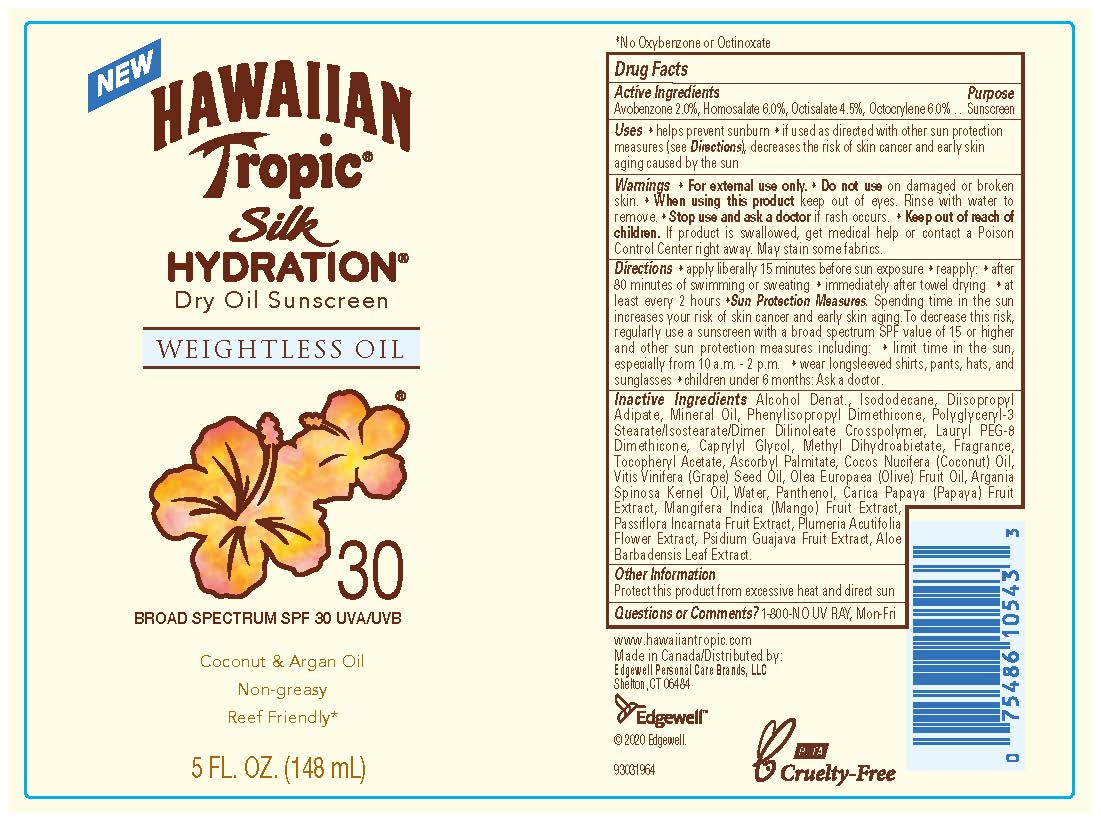 DRUG LABEL: Hawaiin Tropic Silk Hydration Dry Broad Spectrum SPF 30
NDC: 63354-632 | Form: OIL
Manufacturer: Edgewell Personal Care Brands LLC
Category: otc | Type: HUMAN OTC DRUG LABEL
Date: 20241031

ACTIVE INGREDIENTS: OCTOCRYLENE 6 g/100 g; AVOBENZONE 2 g/100 g; HOMOSALATE 6 g/100 g; OCTISALATE 4.5 g/100 g
INACTIVE INGREDIENTS: MINERAL OIL; GRAPE SEED OIL; WATER; LAURYL PEG/PPG-18/18 METHICONE; ASCORBYL PALMITATE; COCONUT OIL; OLIVE OIL; .ALPHA.-TOCOPHEROL ACETATE; ARGAN OIL; PANTHENOL; MANGO; PASSIFLORA INCARNATA FRUIT; GUAVA; ALCOHOL; METHYL DIHYDROABIETATE; ISODODECANE; DIISOPROPYL ADIPATE; CAPRYLYL GLYCOL; PAPAYA; PLUMERIA RUBRA FLOWER; ALOE VERA LEAF

Active ingredients

Avobenzone 2.0%, Homosalate 6.0%, Octisalate 4.5%, Octocrylene 6.0%

Purpose

Sunscreen

Uses

• helps prevent sunburn • if used as directed with other sun protection measures (see Directions), decreases the risk of skin cancer and early skin aging caused by the sun

Warnings

For external use only

May stain some fabrics

Do not use

on damaged or broken skin

When using this product

• Keep out of eyes. Rinse with water to remove.

Stop use and ask a doctor

if rash occurs

Keep out of reach of children

If product is swallowed, get medical help or contact a Poison Control Center right away

Directions

• apply liberally 15 minutes before sun exposure • reapply: • after 80 minutes of swimming or sweating • immediately after towel drying • at least every 2 hours • Sun Protection Measures. Spending time in the sun increases your risk of skin cancer and early skin aging. To decrease this risk, regularly use a sunscreen with a broad spectrum SPF value of 15 or higher and other sun protection measures including: • limit time in the sun, especially from 10 a.m. - 2 p.m. • wear longsleeved shirts, pants, hats, and sunglasses • children under 6 months: Ask a doctor

Inactive Ingredients

Alcohol Denat., Isododecane, Diisopropyl Adipate, Mineral Oil, Phenylisopropyl Dimethicone, Polyglyceryl-3 Stearate/Isostearate/Dimer Dilinoleate Crosspolymer, Lauryl PEG-8 Dimethicone, Caprylyl Glycol, Methyl Dihydroabietate, Fragrance, Tocopheryl Acetate, Ascorbyl Palmitate, Cocos Nucifera (Coconut) Oil, Vitis Vinifera (Grape) Seed Oil, Olea Europaea (Olive) Fruit Oil, Argania Spinosa Kernel Oil, Water, Panthenol, Carica Papaya (Papaya) Fruit Extract, Mangifera Indica (Mango) Fruit Extract, Passiflora Incarnata Fruit Extract, Plumeria Acutifolia Flower Extract, Psidium Guajava Fruit Extract, Aloe Barbadensis Leaf Extract

Other information

Protect this product from excessive heat and direct sun

Questions or Comments?

Call 1-800-NO UV RAY, Mon-Fri

Primary Display Panel

NEW
HAWAIIAN
Tropic (R)

Silk

HYDRATION (R)

Dry Oil Sunscreen

WEIGHTLESS OIL

30

BROAD SPECTRUM SPF 30 UVA/UVB

Coconut & Argan Oil

Non-greasy

Reef Friendly*

5 FL. OZ. (148 mL)